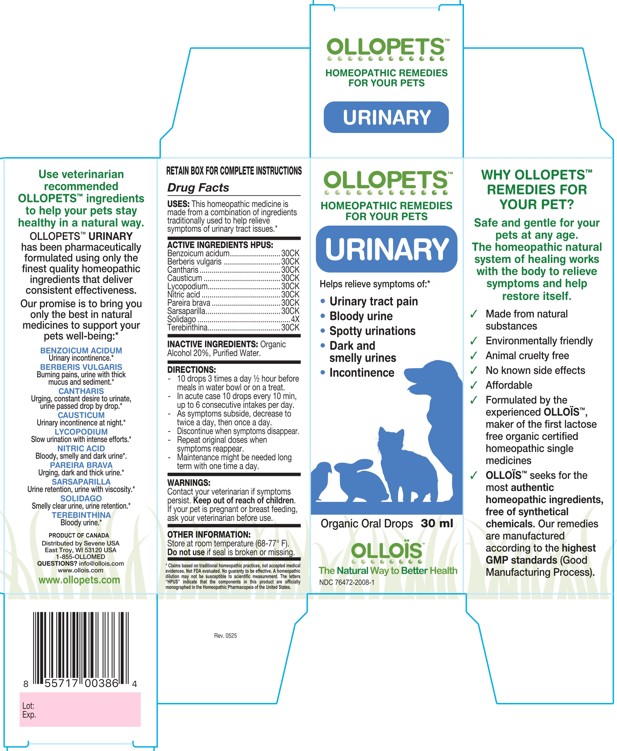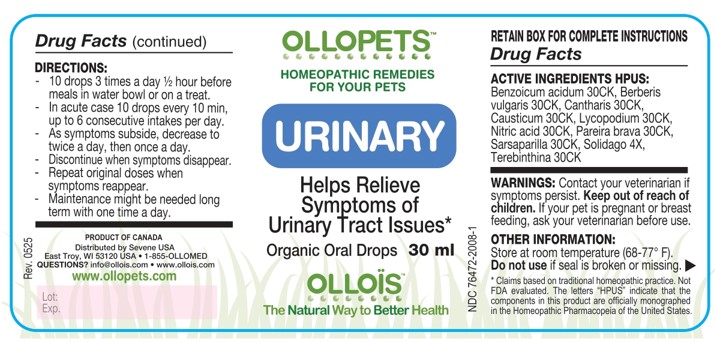 DRUG LABEL: OLLOPETS URINARY
NDC: 76472-2008 | Form: SOLUTION
Manufacturer: SEVENE USA
Category: homeopathic | Type: OTC ANIMAL DRUG LABEL
Date: 20260218

ACTIVE INGREDIENTS: BENZOIC ACID 30 [hp_C]/100 mL; BERBERIS VULGARIS ROOT BARK 30 [hp_C]/100 mL; LYTTA VESICATORIA 30 [hp_C]/100 mL; CAUSTICUM 30 [hp_C]/100 mL; LYCOPODIUM CLAVATUM SPORE 30 [hp_C]/100 mL; Nitric acid 30 [hp_C]/100 mL; CHONDRODENDRON TOMENTOSUM ROOT 30 [hp_C]/100 mL; SMILAX ORNATA ROOT 30 [hp_C]/100 mL; SOLIDAGO CALIFORNICA WHOLE 4 [hp_X]/100 mL; TURPENTINE OIL 30 [hp_C]/100 mL
INACTIVE INGREDIENTS: ALCOHOL; WATER

SEVENE USA - OLLOPETS - URINARY

ACTIVE INGREDIENT HPUS

Benzoicum acidum.........................30CK
Berberis vulgaris ............................30CK
Cantharis ........................................30CK
Causticum ......................................30CK
Lycopodium....................................30CK
Nitric acid .......................................30CK
Pareira brava ..................................30CK
Sarsaparilla.....................................30CK
Solidago ..............................................4X
Terebinthina....................................30CK